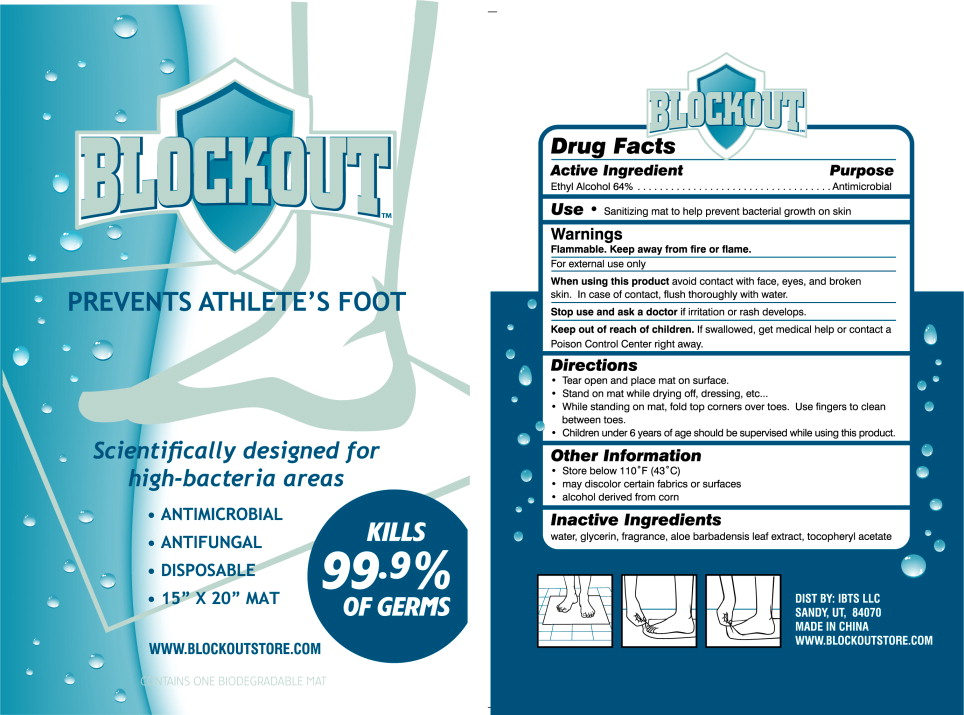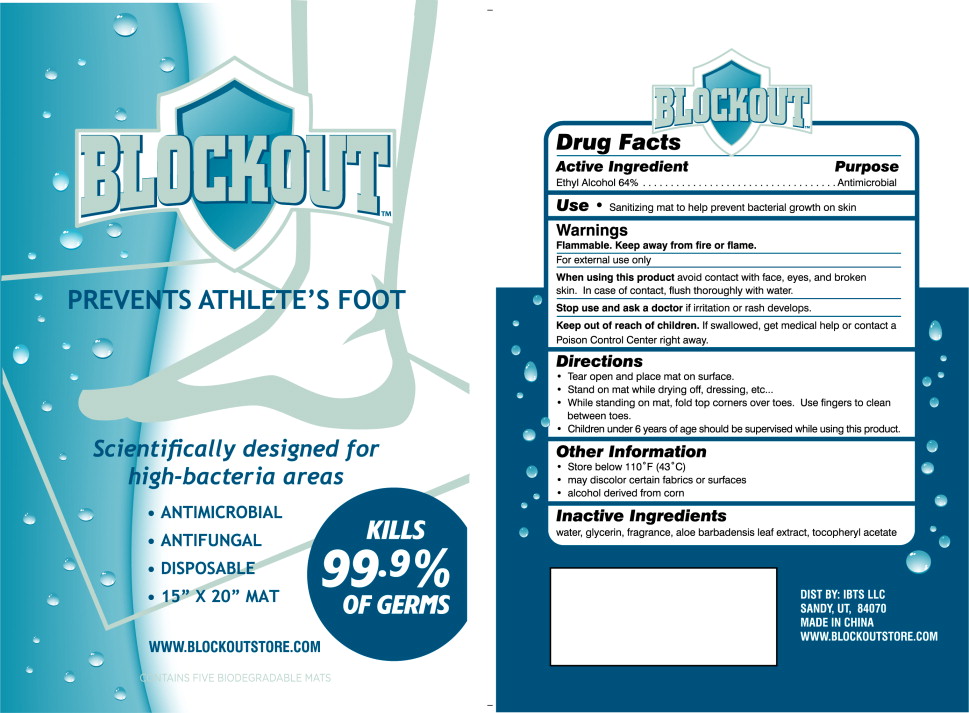 DRUG LABEL: Blockout Foot Wipes
NDC: 51362-1677 | Form: CLOTH
Manufacturer: Ideas Born to Succeed
Category: otc | Type: HUMAN OTC DRUG LABEL
Date: 20100819

ACTIVE INGREDIENTS: ALCOHOL 1 ug/1 mL
INACTIVE INGREDIENTS: POLYSORBATE 20 0.8 mg/1 mL; GLYCERIN 96 mg/1 mL; WATER 870.4 mg/1 mL

BLOCKOUT™

Drug Facts

Active Ingredient

Ethyl Alcohol 64%

Purpose

Antimicrobial

Use

- Sanitizing mat to help prevent bacterial growth on skin

Warnings

Flammable. Keep away from fire or flame.

For external use only

When using this product

avoid contact with face, eyes, and broken skin. In case of contact, flush thoroughly with water.

Stop use and ask a doctor

if irritation or rash develops.

Keep out of reach of children.

If swallowed, get medical help or contact a Poison Control Center right away.

Directions

- Tear open and place mat on surface.
- Stand on mat while drying off, dressing, etc...
- While standing on mat, fold top corners over toes. Use fingers to clean between toes.
- Children under 6 years of age should be supervised while using this product.

Other Information

- Store below 110°F (43°C)
- may discolor certain fabrics or surfaces
- alcohol derived from corn

Inactive Ingredients

water, glycerin, fragrance, aloe barbadensis leaf extract, tocopheryl acetate

DIST BY: IBTS LLC
SANDY, UT, 84070
MADE IN CHINA
WWW.BLOCKOUTSTORE.COM

Principal Display Panel – Packet Label

BLOCKOUT™

PREVENTS ATHLETE'S FOOT

Scientifically designed for high-bacteria areas

- ANTIMICROBIAL
- ANTIFUNGAL
- DISPOSABLE
- 15" X 20" MAT

WWW.BLOCKOUTSTORE.COM

CONTAINS ONE BIODEGRADABLE MAT

KILLS

99.^9 %

OF GERMS

Principal Display Panel – Carton Label

BLOCKOUT™

PREVENTS ATHLETE'S FOOT

Scientifically designed for high-bacteria areas

- ANTIMICROBIAL
- ANTIFUNGAL
- DISPOSABLE
- 15" X 20" MAT

WWW.BLOCKOUTSTORE.COM

CONTAINS FIVE BIODEGRADABLE MATS

KILLS

99.^9 %

OF GERMS